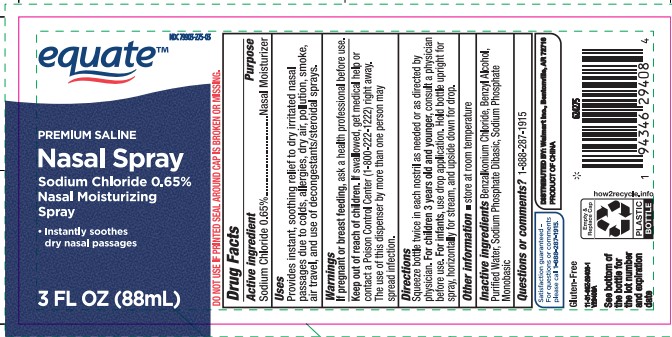 DRUG LABEL: EQUATE PREMIUM SALINE
NDC: 79903-275 | Form: SPRAY
Manufacturer: Walmart Stores, Inc.
Category: otc | Type: HUMAN OTC DRUG LABEL
Date: 20260119

ACTIVE INGREDIENTS: SODIUM CHLORIDE 0.65 g/100 mL
INACTIVE INGREDIENTS: SODIUM PHOSPHATE, DIBASIC, ANHYDROUS; BENZYL ALCOHOL; BENZALKONIUM CHLORIDE; WATER; SODIUM PHOSPHATE, MONOBASIC, ANHYDROUS

Equate Premium Nasal Saline Spray Sodium Chloride 0.65%

Active ingredient

Sodium Chloride 0.65%

Purpose

Nasal Moisturizer

Uses

Provides instant, soothing relief to dry irritated nasal passages due to colds, allergies, dry air, pollution, smoke, air travel, and use of decongestants/steroidal sprays.

Warnings

If pregnant or breast feeding,

ask a health professional before use.

Keep out of reach of children.

If swallowed, get medical help or contact a Poison Control Center (1-800-222-1222) right away. The use of this dispenser by more than one person may spread infection.

Directions

Squeeze bottle twice in each nostril as needed or as directed by physician. For children 3 years old and younger, consult a physician before use. For infants, use drop applicaiton. Hold bottle upright for spray, horizontally for stream, and upside down for drop.

Other information

store at room temperature

Inactive ingredients

Benzalkonium Chloride, Benzyl Alcohol, Purified Water, Sodium Phosphate Dibasic, Sodium Phosphate Monobasic

Questions or comments?

1-888-287-1915